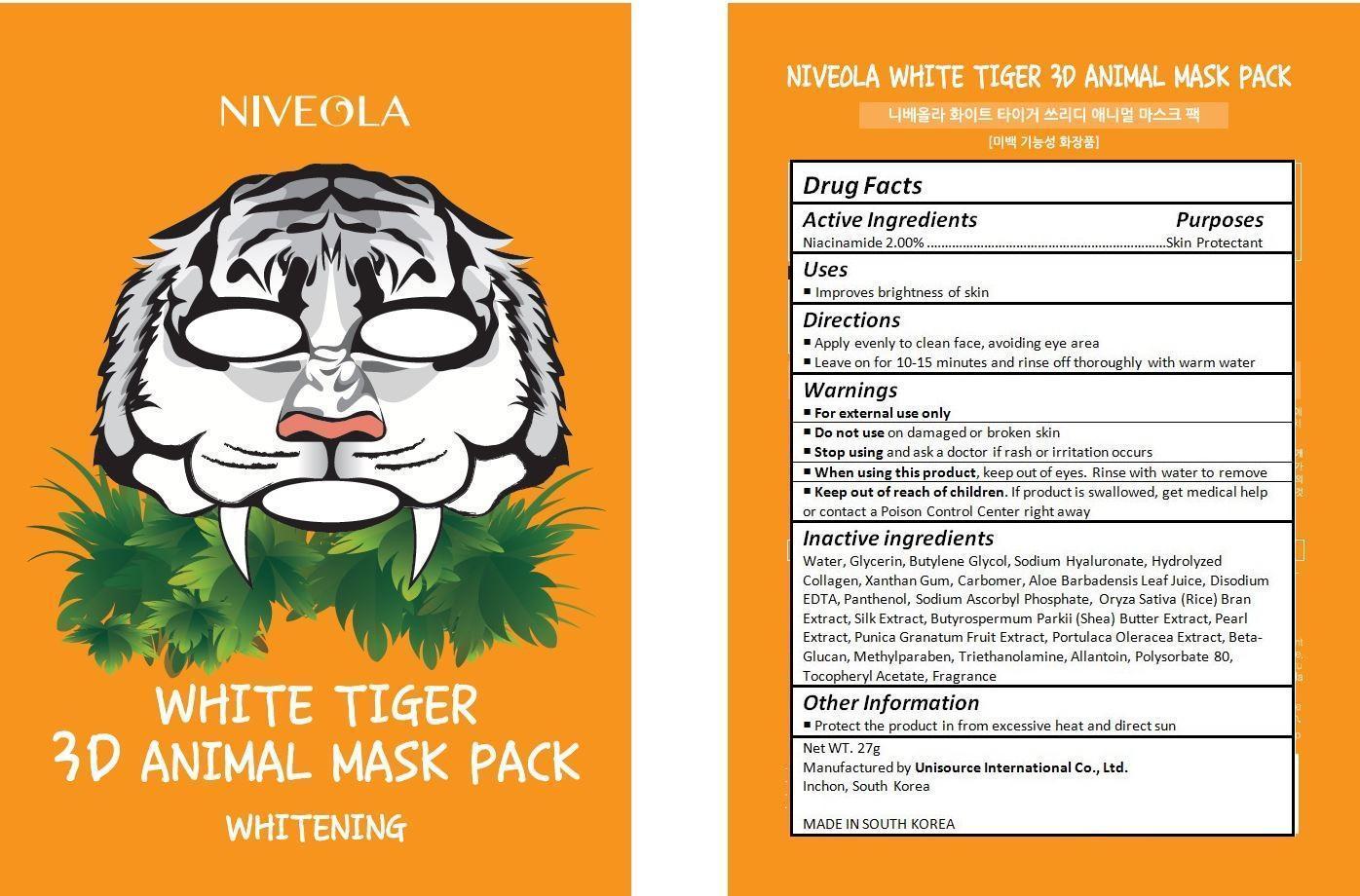 DRUG LABEL: NIVEOLA WHITE TIGER 3D ANIMAL MASK PACK
NDC: 70133-004 | Form: CREAM
Manufacturer: Unisource International Co., Ltd.
Category: otc | Type: HUMAN OTC DRUG LABEL
Date: 20151008

ACTIVE INGREDIENTS: Niacinamide 0.54 g/27 g
INACTIVE INGREDIENTS: WATER; GLYCERIN; BUTYLENE GLYCOL; HYALURONATE SODIUM; XANTHAN GUM; CARBOMER HOMOPOLYMER TYPE C (ALLYL PENTAERYTHRITOL CROSSLINKED); ALOE VERA LEAF; EDETATE DISODIUM; PANTHENOL; SODIUM ASCORBYL PHOSPHATE; RICE BRAN; BOMBYX MORI FIBER; SHEA BUTTER; PEARL (HYRIOPSIS CUMINGII); POMEGRANATE; PURSLANE; CURDLAN; METHYLPARABEN; TROLAMINE; ALLANTOIN; POLYSORBATE 80; .ALPHA.-TOCOPHEROL ACETATE

Drug Facts

ACTIVE INGREDIENT

Niacinamide 2.00%

PURPOSE

Skin Protectant

INDICATIONS AND USAGE

Improves brightness of skin

DOSAGE AND ADMINISTRATION

Apply evenly to clean face, avoiding eye area
Leave on for 10-15 minutes and rinse off thoroughly with warm water

WARNINGS

For external use only.
Do not use on damaged or broken skin.
When using this product, keep out of eyes. Rinse with water to remove.
Stop using and ask a doctor if rash occurs.

KEEP OUT OF REACH OF CHILDREN

Keep out of reach of the children. If product is swallowed, get medical help or contact a poison control center right away.

INACTIVE INGREDIENT

Water, Glycerin, Butylene Glycol, Sodium Hyaluronate, Hydrolyzed Collagen, Xanthan Gum, Carbomer, Aloe Barbadensis Leaf Juice, Disodium EDTA, Panthenol, Sodium Ascorbyl Phosphate, Oryza Sativa (Rice) Bran Extract, Silk Extract, Butyrospermum Parkii (Shea) Butter Extract, Pearl Extract, Punica Granatum Fruit Extract, Portulaca Oleracea Extract, Beta-Glucan, Methylparaben, Triethanolamine, Allantoin, Polysorbate 80, Tocopheryl Acetate, Fragrance